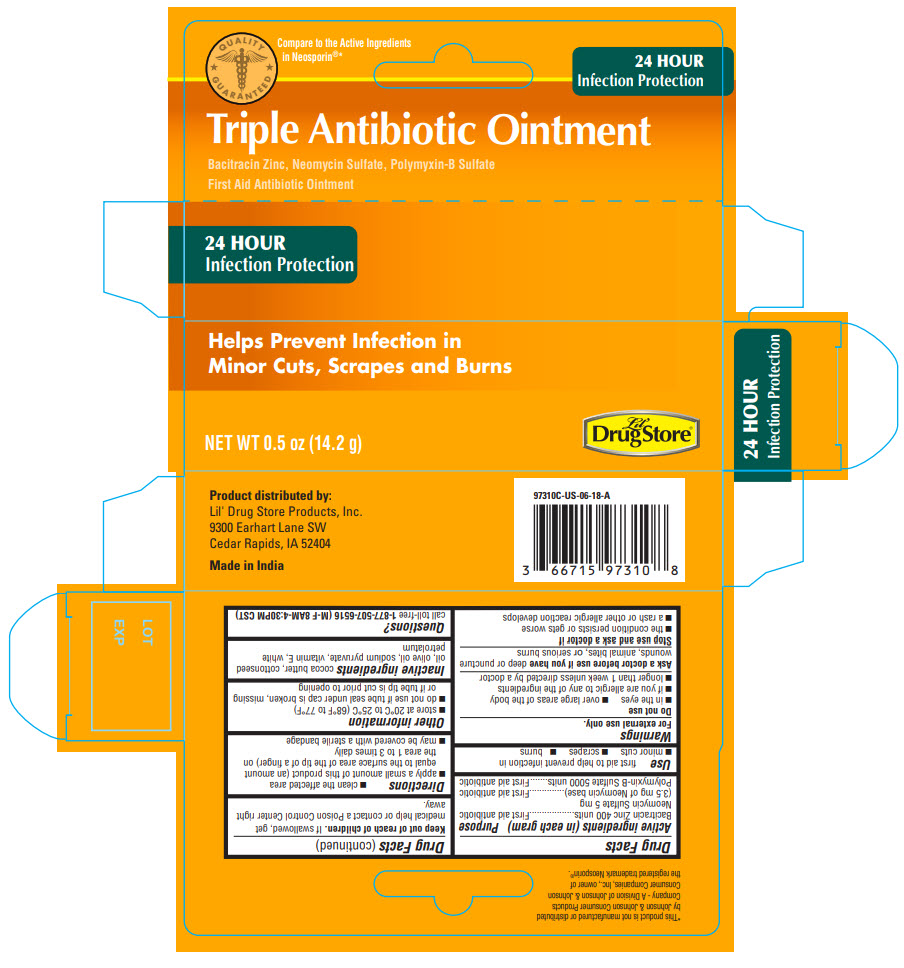 DRUG LABEL: Triple Antibiotic
NDC: 66715-9731 | Form: OINTMENT
Manufacturer: Lil' Drug Store Products, Inc.
Category: otc | Type: HUMAN OTC DRUG LABEL
Date: 20231215

ACTIVE INGREDIENTS: BACITRACIN ZINC 400 [iU]/1 g; POLYMYXIN B SULFATE 5000 [iU]/1 g; NEOMYCIN SULFATE 3.5 mg/1 g
INACTIVE INGREDIENTS: COCOA BUTTER; COTTONSEED OIL; OLIVE OIL; SODIUM PYRUVATE; .ALPHA.-TOCOPHEROL ACETATE; PETROLATUM

Triple Antibiotic Ointment

Drug Facts

ACTIVE INGREDIENT

Active ingredients (in each gram) | Purpose
Bacitracin Zinc 400 units | First aid antibiotic
Neomycin Sulfate 5 mg (3.5 mg of Neomycin base) | First aid antibiotic
Polymyxin-B Sulfate 5000 units | First aid antibiotic

Use

first aid to help prevent infection in

- minor cuts
- scrapes
- burns

Warnings

For external use only.

Do not use

- in the eyes
- over large areas of the body
- if you are allergic to any of the ingredients
- longer than 1 week unless directed by a doctor

Ask a doctor before use if you have deep or puncture wounds, animal bites, or serious burns

Stop use and ask a doctor if

- the condition persists or gets worse
- a rash or other allergic reaction develops

Keep out of reach of children. If swallowed, get medical help or contact a Poison Control Center right away.

Directions

- clean the affected area
- apply a small amount of this product (an amount equal to the surface area of the tip of a finger) on the area 1 to 3 times daily
- may be covered with a sterile bandage

Other information

- store at 20°C to 25°C (68°F to 77°F)
- do not use if tube seal under cap is broken, missing or if tube tip is cut prior to opening

Inactive ingredients

cocoa butter, cottonseed oil, olive oil, sodium pyruvate, vitamin E, white petrolatum

Questions?

call toll-free 1-877-507-6516 (M-F 8AM-4:30PM CST)

Product distributed by:
Lil' Drug Store Products, Inc.
9300 Earhart Lane SW
Cedar Rapids, IA 52404

PRINCIPAL DISPLAY PANEL - 14.2 g Tube Carton

QUALITY
GUARANTEED

Compare to the Active Ingredients
in Neosporin®*

24 HOUR
Infection Protection

Triple Antibiotic Ointment

Bacitracin Zinc, Neomycin Sulfate, Polymyxin-B Sulfate
First Aid Antibiotic Ointment

Helps Prevent Infection in
Minor Cuts, Scrapes and Burns

NET WT 0.5 oz (14.2 g)

Lil'
Drug Store®